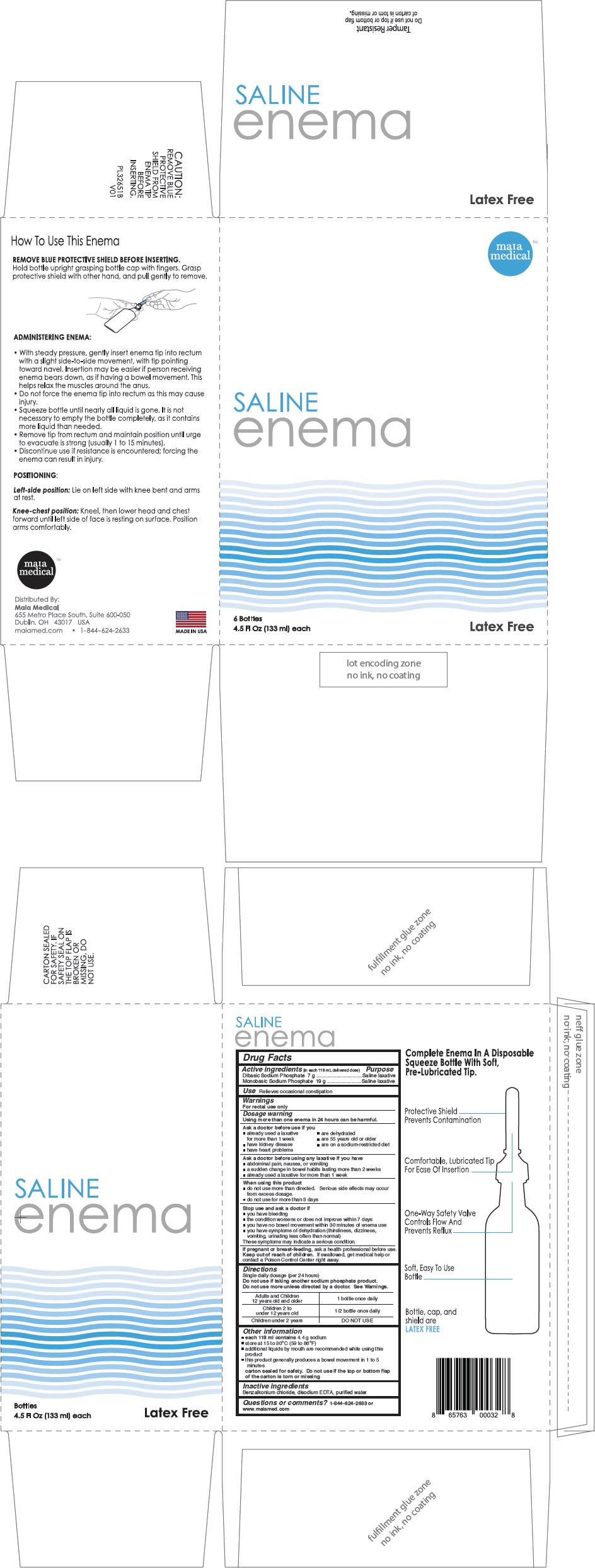 DRUG LABEL: QUALITY CHOICE SINGLE SALINE 
NDC: 71443-001 | Form: ENEMA
Manufacturer: Alcyon Health, LLC.
Category: otc | Type: HUMAN OTC DRUG LABEL
Date: 20170712

ACTIVE INGREDIENTS: SODIUM PHOSPHATE, DIBASIC, UNSPECIFIED FORM 7 g/118 mL; SODIUM PHOSPHATE, MONOBASIC, UNSPECIFIED FORM 19 g/118 mL
INACTIVE INGREDIENTS: BENZALKONIUM CHLORIDE; EDETATE DISODIUM; WATER

QUALITY CHOICE SINGLE SALINE ENEMA
LAXATIVE

Drug Facts

ACTIVE INGREDIENT

PURPOSE

Active ingredients (in each 118 mL delivered dose) | Purpose
Dibasic Sodium Phosphate 7 g | Saline laxative
Monobasic Sodium Phosphate 19 g | Saline laxative

Use

Relieves occasional constipation

Warnings

For rectal use only

Dosage warning

Using more than one enema in 24 hours can be harmful.

Ask a doctor before use if you

- already used a laxative for more than 1 week
- are dehydrated
- have kidney disease
- are 55 years old or older
- have heart problems
- are on a sodium-restricted diet

Ask a doctor before using any laxative if you have

- abdominal pain, nausea, or vomiting
- a sudden change in bowel habits lasting more than 2 weeks
- already used a laxative for more than 1 week

When using this product

- do not use more than directed. Serious side effects may occur from excess dosage.
- do not use for more than 3 days

Stop use and ask a doctor if

- you have bleeding
- the condition worsens or does not improve within 7 days
- you have no bowel movement within 30 minutes of enema use
- you have symptoms of dehydration (thirstiness, dizziness, vomiting, urinating less often than normal)

These symptoms may indicate a serious condition.

PREGNANCY OR BREAST FEEDING

If pregnant or breast-feeding, ask a health professional before use.

Keep out of reach of children. If swallowed, get medical help or contact a Poison Control Center right away.

Directions

Single daily dosage (per 24 hours)

Do not use if taking another sodium phosphate product.

Do not use more unless directed by a doctor. See Warnings.

Adults and Children 12 years old and older | 1 bottle once daily
Children 2 to under 12 years old | 1/2 bottle once daily
Children under 2 years | DO NOT USE

Other information

- each 118 ml contains 4.4 g sodium
- store at 15 to 30°C (59 to 86°F)
- additional liquids by mouth are recommended while using this product
- this product generally produces a bowel movement in 1 to 5 minutes
  carton sealed for safety. Do not use if the top or bottom flap of the carton is torn or missing

Inactive ingredients

Benzalkonium chloride, disodium EDTA, purified water

Questions or comments?

1-844-624-2633 or www.maiamed.com

Distributed By:
Maia Medical
655 Metro Place South, Suite 600-050
Dublin, OH 43017 USA

PRINCIPAL DISPLAY PANEL - 133 ml Bottle Carton

maia
medical™

SALINE
enema

6 Bottles
4.5 Fl Oz (133 ml) each

Latex Free